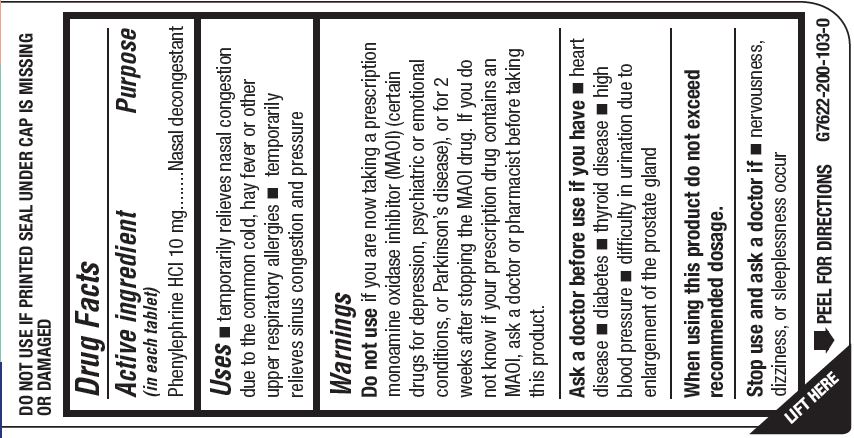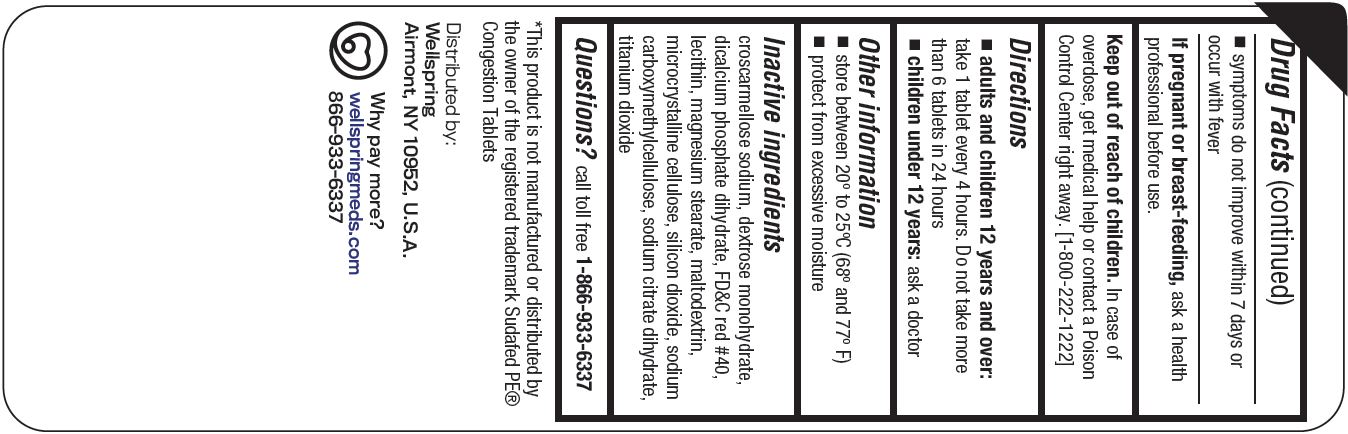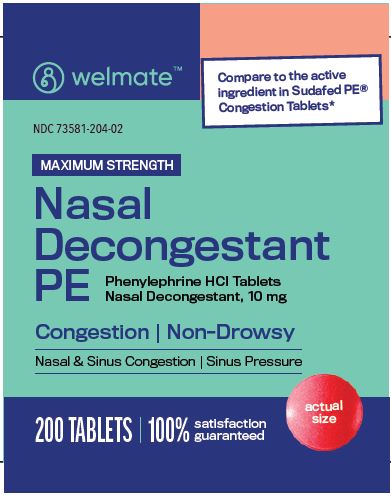 DRUG LABEL: NASAL DECONGESTANT PE
NDC: 73581-204 | Form: TABLET
Manufacturer: YYBA CORP
Category: otc | Type: HUMAN OTC DRUG LABEL
Date: 20240103

ACTIVE INGREDIENTS: PHENYLEPHRINE HYDROCHLORIDE 25 mg/1 1
INACTIVE INGREDIENTS: CROSCARMELLOSE SODIUM; DEXTROSE MONOHYDRATE; DIBASIC CALCIUM PHOSPHATE DIHYDRATE; FD&C RED NO. 40; LECITHIN, SUNFLOWER; MAGNESIUM STEARATE; MALTODEXTRIN; MICROCRYSTALLINE CELLULOSE; SILICON DIOXIDE; SODIUM CARBOXYMETHYL .BETA.-GLUCAN (DS 0.65-0.85); TRISODIUM CITRATE DIHYDRATE; TITANIUM DIOXIDE

YYBA (as PLD) - WELMATE - Nasal Decongestant PE Tablets, 10 MG (73581-204)

Active ingredient (in each tablet)

Phenylephrine HCL 10 mg

Purpose

Nasal decongestant

Uses

- temporarily relieves nasal congestion due to the common cold, hay fever or other upper respiratory allergies

- temporarily relieves sinus congestion and pressure

Warnings

Do not useif you are taking a prescription monoamine oxidase inhibitor (MA0l)(certain drugs for depression, psychiatric or emotional conditions, or Parkinson's disease), or for 2 weeks after stopping the MA0l drug. If you do not know if your prescription drug contains an MA0l, ask a doctor or pharmacist before taking this product.

Ask a doctor before use if you have

- heart disease
- diabetes
- thyroid disease
- high blood pressure
- difficulty in urination due to enlargement of the prostate gland

When using this product do not exceed recommended dosage.

Stop use and ask a doctor if

- nervousness, dizziness, or sleeplessness occur
- symptoms do not improve within 7 days or occur with fever

If pregnant or breast-feeding,as a health professional before use.

Keep out of reach of children.In case of overdose, get medical help or contact a Poison Control Center right away [1-800-222-1222]

Directions

- adults and children 12 years and older:

take 1 tablet 4 hours. Do not take more than 6 tablets in 24 hours

- children under 12 years:ask a doctor

Other information

- store between 20° and 25°C (68° and 77°F)
- protect from excessive moisture

Inactive ingredients

croscarmellose sodium, dextrose monohydrate, dicalcium phosphate dihydrate, FD&C red #40. lecithin, magnesium stearate, maltrodextrin, microcrystalline cellulose, silicon dioxide, sodium carboxymethylcellulose, sodium citrate dihydrate, titanium dioxide

Questions?

call toll-free 1-866-933-6337